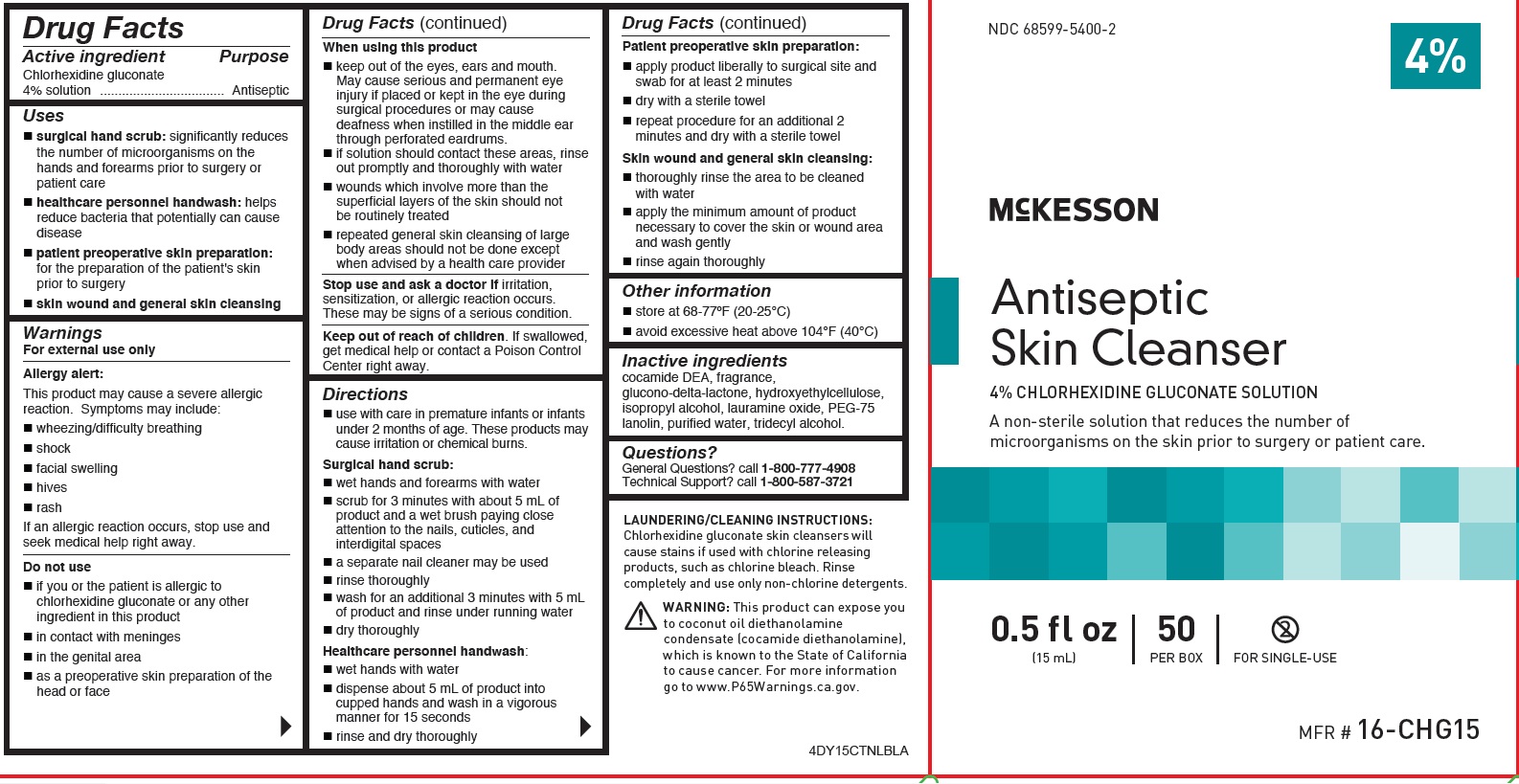 DRUG LABEL: CHLORHEXIDINE GLUCONATE
NDC: 68599-5400 | Form: GEL
Manufacturer: McKesson
Category: otc | Type: HUMAN OTC DRUG LABEL
Date: 20251219

ACTIVE INGREDIENTS: CHLORHEXIDINE GLUCONATE 4 g/100 mL
INACTIVE INGREDIENTS: TRIDECYL ALCOHOL; COCO DIETHANOLAMIDE; PEG-75 LANOLIN; GLUCONOLACTONE; HYDROXYETHYL CELLULOSE (100 MPA.S AT 2%); LAURAMINE OXIDE; WATER; ISOPROPYL ALCOHOL

McKesson Antiseptic Skin Cleanser

Drug Facts

Active ingredient
Chlorhexidine gluconate 4% solution

Purpose
Antiseptic

Uses

- Surgical hand scrub:significantly reduces the number of microorganisms on the hands and forearms prior to surgery or patient care.
- Healthcare personnel handwash: helps reduce bacteria that potentially can cause disease
- Patient preoperative skin preparation:for the preparation of the patient's skin prior to surgery skin wound and general skin cleansing
- Skin wound and general skin cleansing

Warnings
For external use only
Allergy Alert
This product may cause a severe allergic reaction. Symptoms may include:

- wheezing/difficulty breathing
- shock
- facial swelling
- hives
- rash

WARNING: This product can expose you
to coconut oil diethanolamine
condensate (cocamide diethanolamine),
which is known to the State of California
to cause cancer. For more information
go to www.P65Warnings.ca.gov.

STOP USE

If an allergic reaction occurs, stop use and seek medical help right away.
Do not use

- if you are allergic to chlorhexidine gluconate or any other ingredients in this product
- in contact with meninges
- in the genital area
- as a preoperative skin preparation of the head or face

When using this product

- keep out of eyes, ears, and mouth. May cause serious and permanent eye injury if placed or kept in the eye during surgical procedures or may cause deafness when instilled in the middle ear through perforated eardrums
- if solution should contact these areas, rinse out promptly and thoroughly with water
- wounds which involve more than the superficial layers of the skin should not be routinely treated
- repeated general skin cleansing of large body areas should not be done except when the underlying

condition makes it necessary to reduce the bacterial population of the skin
Stop use and ask doctor ifirritation, sensitization or allergic reaction occurs. These may be signs of a serious condition.

Keep out of reach of children.If swallowed, get medical help or contact a Poison Control Center right away.

Directions

- use with care in premature infants or infants under 2 months of age. These products may causeirritation or chemical burns.

Surgical hand s crub:

- wet hands and forearms with water
- scrub for 3 minutes with about 5 mL of product and a wet brush paying close attention to the nails, cuticles, and interdigital spaces
- a separate nail cleaner may be used
- rinse thoroughly
- wash for an additional 3 minutes with 5 mL of product and rinse under running water
- dry thoroughly

Healthcare personnel handwash:

- wet hands with water
- dispense about 5 mL of product into cupped hands and wash in a vigorous manner for 15 seconds
- rinse and dry thoroughly

Patient preoperative skin preparation:

- apply product liberally to surgical site and swab for at least 2 minutes and dry with a sterile towel
- repeat procedure for an additional 2 minutes and dry with a sterile towel

Skin wound and general skin cleaning:

- thoroughly rinse the area to be cleaned with water
- apply the minimum amount of product necessary to cover the skin or wound area and wash gently
- rinse again thoroughly

Other information

- store at 68-77ºF (20-25°C)
- avoid excessive heat above 104°F (40°C)

Inactive ingredients
cocamide DEA, fragrance, glucono-delta-lactone, hydroxyethylcellulose, isopropyl alcohol, lauramine
oxide, PEG-75 lanolin, purified water, tridecyl alcohol

Questions?
General Questions? Call 1-800-777-4908
Technical Support? Call 1-800-587-3721

PACKAGE LABEL

NDC 68599-5400-2
McKesson
Antiseptic Skin Cleanser
4% CHLORHEXIDINE GLUCONATE SOLUTION
A non-sterile solution that reduces the number of
microorganisms on the skin prior to surgery or patient care.
0.5 fl oz
(15 mL)
50
PER BOX
FOR SINGLE-USE
MFR # 16-CHG15